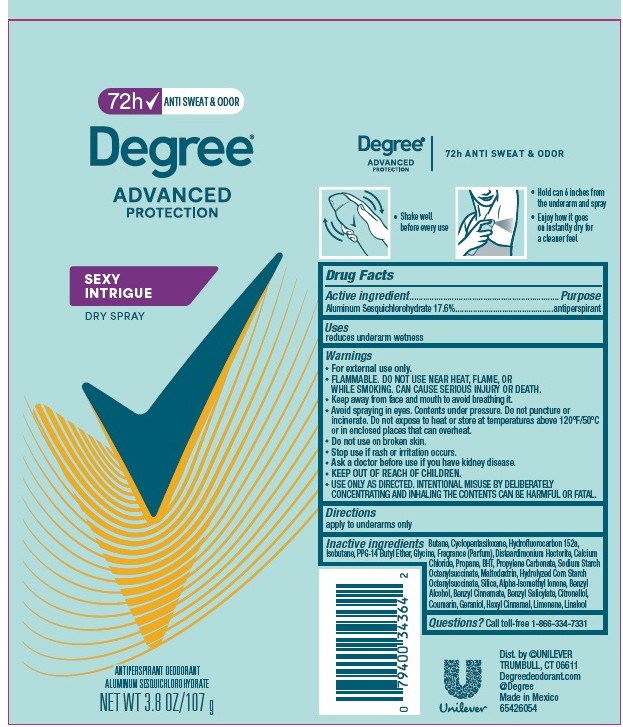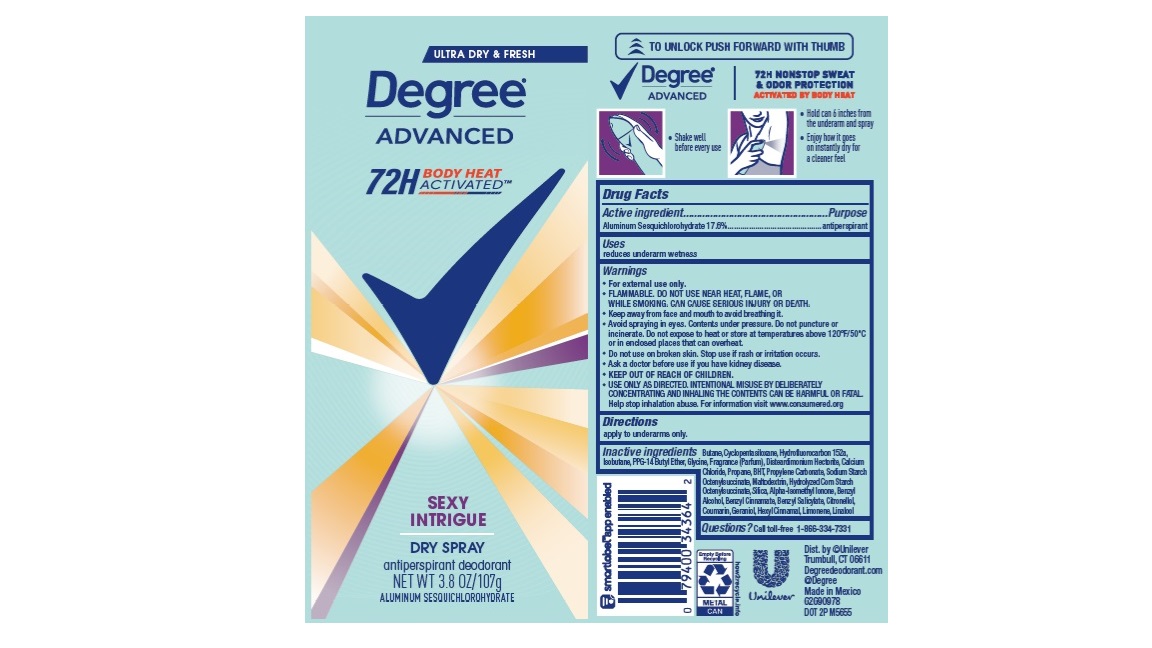 DRUG LABEL: Degree
NDC: 64942-2255 | Form: AEROSOL, SPRAY
Manufacturer: Conopco, Inc. d/b/a Unilever
Category: otc | Type: HUMAN OTC DRUG LABEL
Date: 20260210

ACTIVE INGREDIENTS: ALUMINUM SESQUICHLOROHYDRATE 17.6 g/100 g
INACTIVE INGREDIENTS: HYDROXYCITRONELLAL; LINALOOL, (+/-)-; BENZYL SALICYLATE; BENZYL ALCOHOL; PROPYLENE CARBONATE; SILICON DIOXIDE; MALTODEXTRIN; COUMARIN; GLYCINE; ISOBUTANE; .BETA.-CITRONELLOL, (R)-; BUTANE; 1,1-DIFLUOROETHANE; CYCLOMETHICONE 5; PPG-14 BUTYL ETHER; DISTEARDIMONIUM HECTORITE; CALCIUM CHLORIDE; PROPANE; BUTYLATED HYDROXYTOLUENE; GERANIOL; ISOMETHYL-.ALPHA.-IONONE; .ALPHA.-HEXYLCINNAMALDEHYDE; LIMONENE, (+)-

Degree Advanced Sexy Intrigue Dry Spray 72H Antiperspirant Deodorant

Drug Facts

Active ingredient

Aluminum Sesquichlorohydrate (17.6%)

Purpose

antiperspirant

Uses

reduces underarm wetness

Directions

For underarms use only

Inactive ingredients

Butane, Cyclopentasiloxane, Hydrofluorocarbon 152a,, Isobutane, PPG-14 Butyl Ether, Glycine, Fragrance (Parfum), Disteardimonium Hectorite, Calcium Chloride, Propane, BHT, Propylene Carbonate, Sodium Starch Octenylsuccinate, Maltodextrin, Hydrolyzed Corn Starch Octenylsuccinate, Silica, Alpha-Isomethyl Ionone, Benzyl Alcohol, Benzyl Cinnamate, Benzyl Salicylate, Citronellol, Courmain, Geraniol, Hexyl Cinnamal, Limonene, Linalool

Questions?

Call toll-free 1-866-334-7331